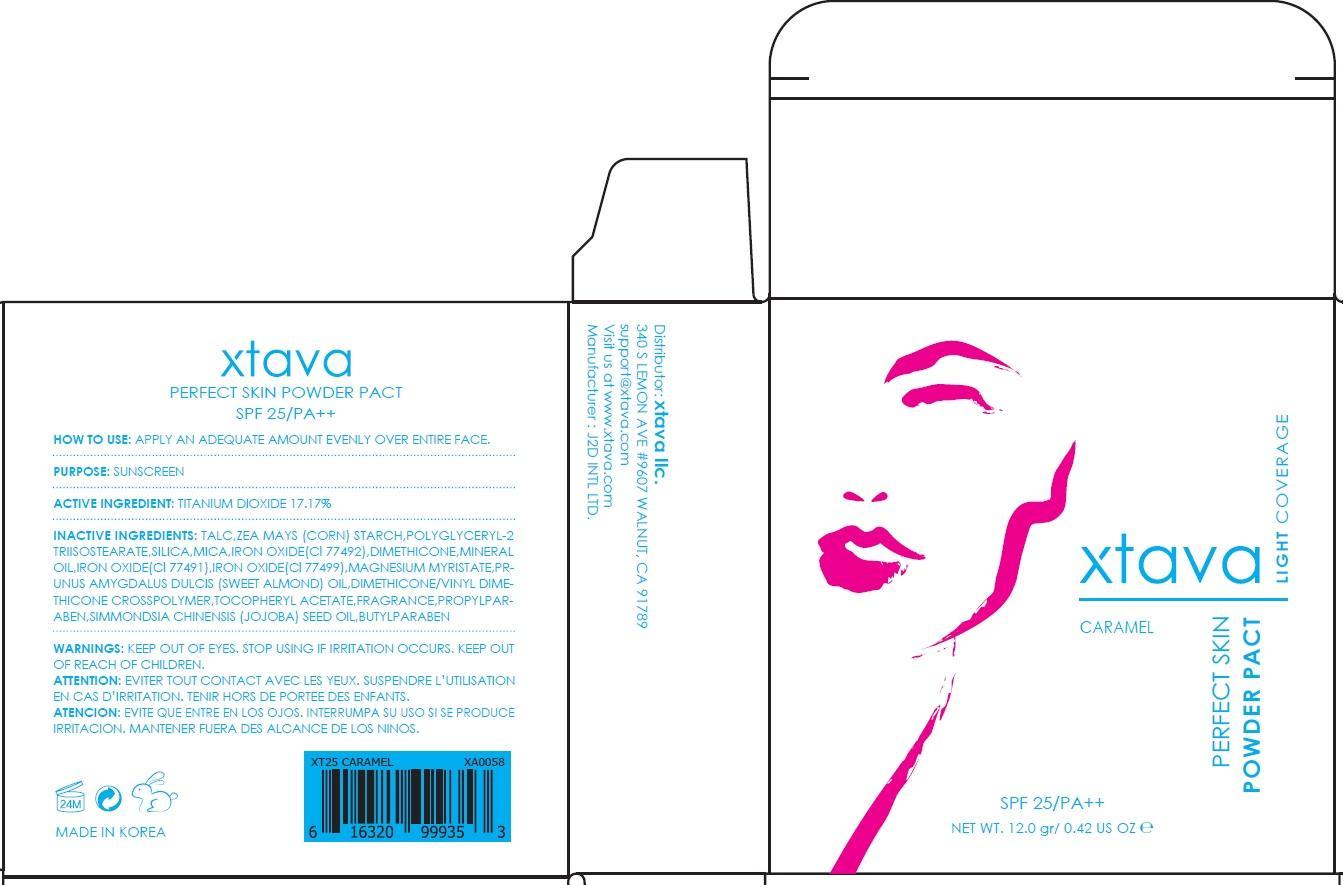 DRUG LABEL: PERFECT SKIN PACT CARAMEL
NDC: 69958-110 | Form: POWDER
Manufacturer: J2D INTERNATIONAL
Category: otc | Type: HUMAN OTC DRUG LABEL
Date: 20150716

ACTIVE INGREDIENTS: Titanium Dioxide 2.06 g/12 g
INACTIVE INGREDIENTS: TALC; POLYGLYCERYL-2 TRIISOSTEARATE

ACTIVE INGREDIENT

Active Ingredient: Titanium Dioxide 17.17%

INACTIVE INGREDIENT

Inactive Ingredients: TALC, ZEA MAYS (CORN) STARCH, POLYGLYCERYL-2 TRIISOSTEARATE, SILICA, MICA, IRON OXIDE(Cl 77492), DIMETHICONE, MINERAL OIL, IRON OXIDE(Cl 77491), IRON OXIDE(Cl 77499), MAGNESIUM MYRISTATE, PRUNUS AMYGDALUS DULCIS (SWEET ALMOND) OIL, DIMETHICONE/VINYL DIMETHICONE CROSSPOLYMER, TOCOPHERYL ACETATE, PERFUME, PROPYLPARABEN, SIMMONDSIA CHINENSIS (JOJOBA) SEED OIL, BUTYLPARABEN

PURPOSE

Purpose: Sunscreen

WARNINGS

Warnings: KEEP OUT OF EYES. STOP USING IF IRRITATION OCCURS. KEEP OUT OF REACH OF CHILDREN.

DESCRIPTION

ATTENTION: EVITER TOUT CONTACT AVEC LES YEUX. SUSPENDRE L’UTILISATION EN CAS D’IRRITATION. TENIR HORS DE PORTEE DES ENFANTS.

ATENCION: EVITE QUE ENTRE EN LOS OJOS. INTERRUMPA SU USO SI SE PRODUCE IRRITACION. MANTENER FUERA DES ALCANCE DE LOS NINOS.

How to use: APPLY AN ADEQUATE AMOUNT EVENLY OVER ENTIRE FACE.